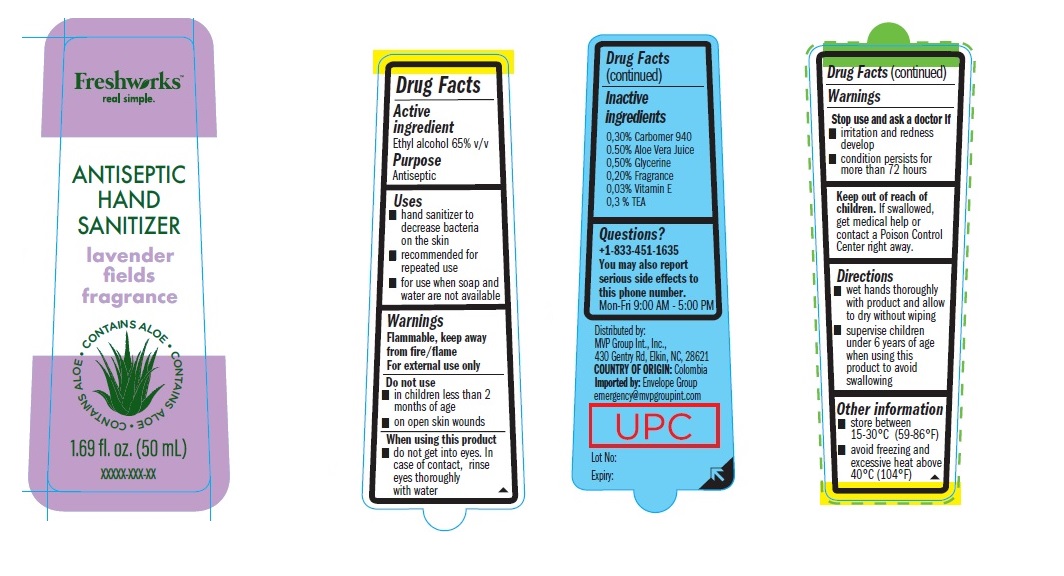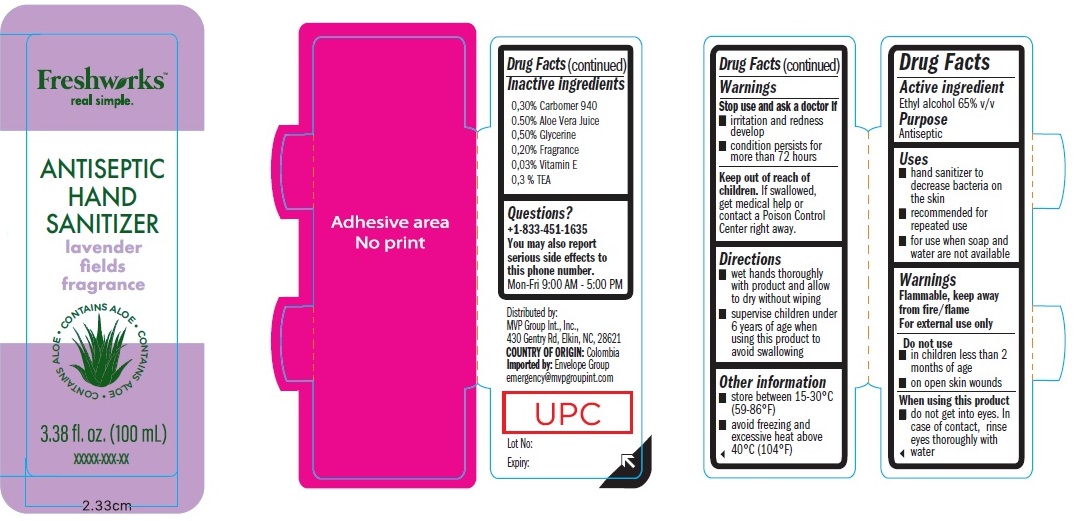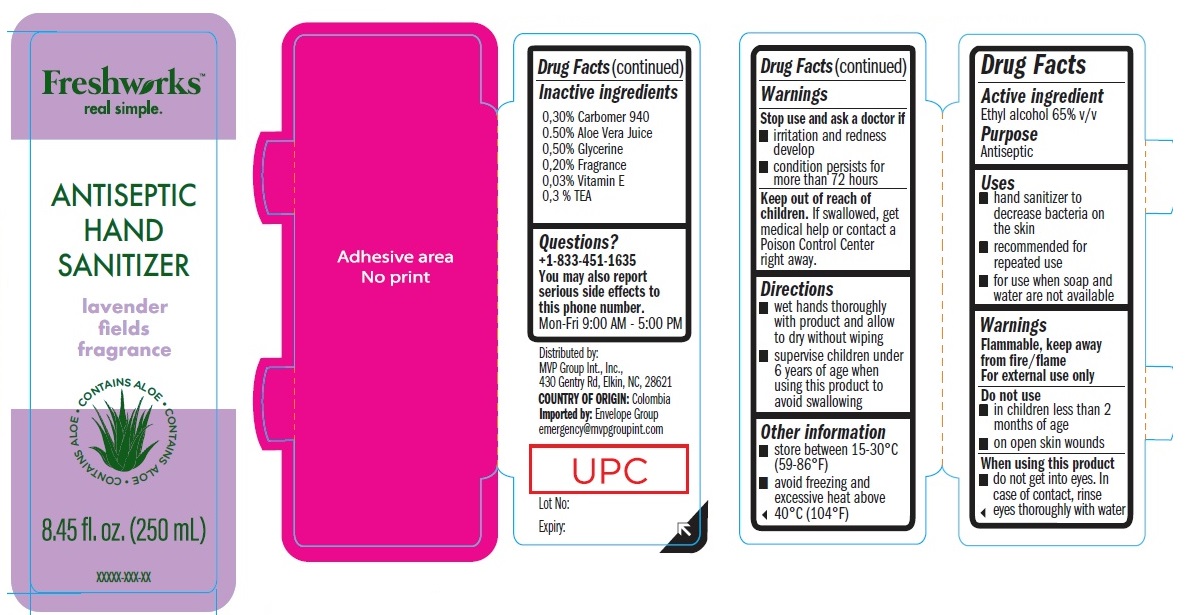 DRUG LABEL: Freshworks Antiseptic Hand Sanitizer Lavender Fields Fragrance
NDC: 80890-002 | Form: GEL
Manufacturer: Envelope Group, LLC
Category: otc | Type: HUMAN OTC DRUG LABEL
Date: 20201208

ACTIVE INGREDIENTS: ALCOHOL 0.65 mL/1 mL
INACTIVE INGREDIENTS: CARBOMER HOMOPOLYMER TYPE C (ALLYL PENTAERYTHRITOL CROSSLINKED); ALOE VERA LEAF; GLYCERIN; .ALPHA.-TOCOPHEROL; TEA LEAF

Freshworks Antiseptic Hand Sanitizer Lavender Fields Fragrance

Active ingredient

Ethyl alcohol 65% v/v

Purpose

Antiseptic

Uses

- hand sanitizer to decrease bacteria on the skin
- recommended for repeated use
- for use when soap and water are not available

Warnings

Flammable, keep away from fire/flame For external use only

Do not use

- in children less than 2 months of age
- on open skin wounds

When using this product

do not get into eyes. In case of contact, rinse eyes thoroughly with water

Stop use and ask a doctor if

- irritation and redness develop
- condition persists for more than 72 hours

Keep out of reach of children.

If swallowed, get medical help or contact a Poison Control Center right away.

Directions

- wet hands thoroughly with product and allow to dry without wiping
- supervise children under 6 years of age when using this product to avoid swallowing

Other information

- store between 15-30°C (59-86°F)
- avoid freezing and excessive heat above 40°C (104°F)

Inactive ingredients

0,30% Carbomer 940 0.50% Aloe Vera Juice 0,50% Glycerine 0,20% Fragrance 0,03% Vitamin E 0,3 % TEA

Questions?

+1-833-451-1635 You may also report serious side effects to this phone number. Mon-Fri 9:00 AM - 5:00 PM